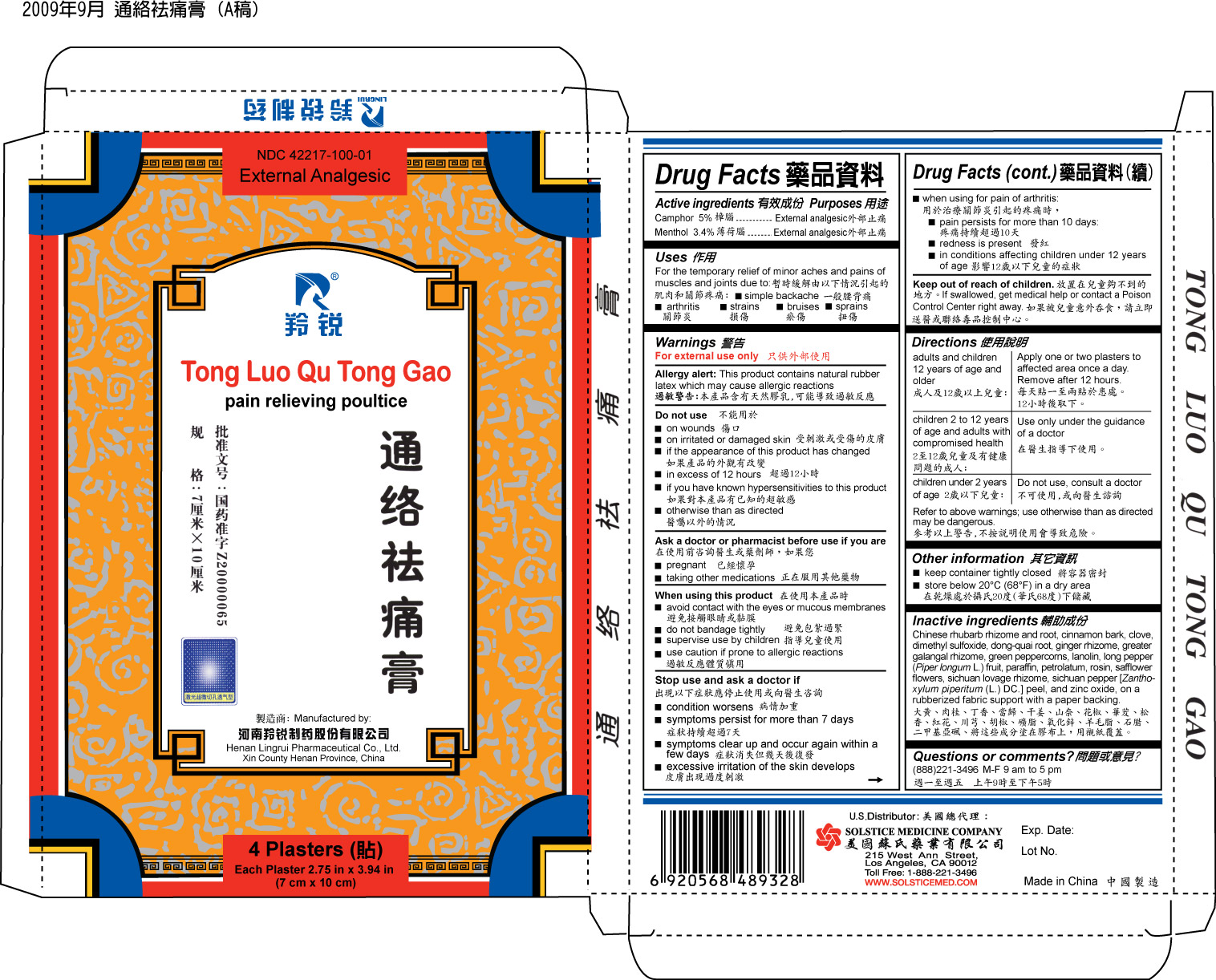 DRUG LABEL: TONG LUO QU TONG GAO
NDC: 42217-100 | Form: POULTICE
Manufacturer: HENAN LINGRUI PHARMACEUTICAL CO LTD
Category: otc | Type: HUMAN OTC DRUG LABEL
Date: 20100602

ACTIVE INGREDIENTS: CAMPHOR (NATURAL) 5 g/1 1; MENTHOL 3.4 g/1 1

DRUG LISTING

Active ingredients
Camphor 5%
Menthol 3.4%

Purposes

External Analgesic

Uses For the temporary relief of minor aches and pains of muscles and joints due to:

- simple backache
- arthritis
- strains
- bruises
- sprains

Do not use

- on wounds
- on irritated or damaged skin
- if the appearance of this product has changed
- in excess of 12 hours
- if you have known hypersensitivities to this product
- otherwise than as directed

Ask a doctor or pharmacist before use if you are

- pregnant
- taking other medications

When using this product

- avoid contact with the eyes or mucous membranes
- do not bandage tightly
- supervise use by children
- use caution if prone to allergic reactions

Stop use and ask a doctor if

- condition worsens
- symptoms persist for more than 7 days
- symptoms clear up and occur again within a few days
- excessive irritation of the skin develops
- when using for pain of arthritis:
-
  - pain persists for more than 10 days
  - redness is present
  - in conditions affecting children under 12 years of age

Keep out of reach of children. If swallowed, get medical help or contact a Poison
Control Center right away.

Directions

- adults and children 12 years of age and older: Apply one or two plasters to affected area once a day. Remove after 12 hours.
- children 2 to 12 years of age and adults with compromised health: Use only under the guidance of a doctor
- children under 2 years of age: Do not use, consult a doctor

Refer to the above warnings; use otherwise than as directed may be dangerous.

Other information

- keep container tightly closed
- store below 20º C (68E F) in a dry area

INACTIVE INGREDIENT

Inactive ingredients Chinese rhubarb rhizome and root, cinnamon bark, clove,
dimethyl sulfoxide, dong-quai root, ginger rhizome, greater galangal rhizome, green
peppercorns, lanolin, long pepper (Piper longum L.) fruit, paraffin, petrolatum, rosin,
safflower flowers, Sichuan lovage rhizome, Sichuan pepper [Zanthoxylum piperitum (L.)
DC.] peel, and zinc oxide, on a rubberized fabric support with a paper backing.

Questions or comments? (888) 221-3496 M-F 9 am to 5 pm

PACKAGE LABEL

TONG LUO QU TONG GAO PAIN RELIEVING POULTICE NDC 44217-100-01 4 PLASTERS EACH PLASTER 2.75 IN X 3.94 IN (7 CM X 10 CM)